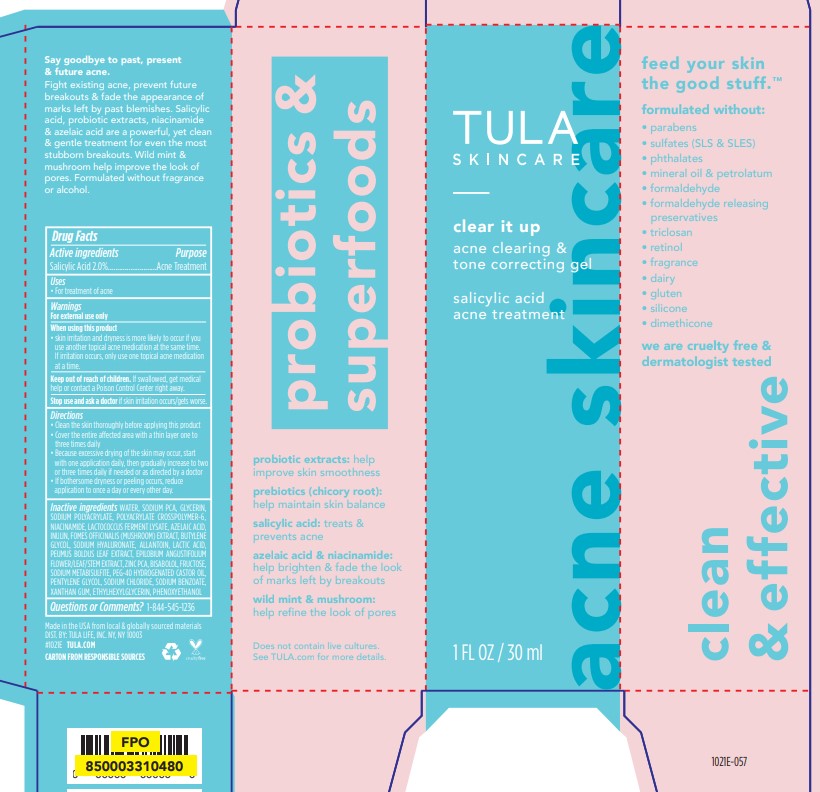 DRUG LABEL: Tula Skincare Clear It Up Acne Clearing and Tone Correcting Gel
NDC: 84126-121 | Form: GEL
Manufacturer: The Procter & Gamble Manufacturing Company
Category: otc | Type: HUMAN OTC DRUG LABEL
Date: 20250529

ACTIVE INGREDIENTS: SALICYLIC ACID 2 g/100 mL
INACTIVE INGREDIENTS: INULIN; SODIUM HYALURONATE; ALLANTOIN; PEUMUS BOLDUS LEAF; LACTIC ACID; FRUCTOSE; XANTHAN GUM; AZELAIC ACID; BISABOLOL; PEG-40 HYDROGENATED CASTOR OIL; PHENOXYETHANOL; WATER; GLYCERIN; SODIUM BENZOATE; ZINC PCA; POLYACRYLATE CROSSPOLYMER-6; BUTYLENE GLYCOL; EPILOBIUM ANGUSTIFOLIUM FLOWERING TOP; ETHYLHEXYLGLYCERIN; SODIUM PCA; SODIUM POLYACRYLATE (8000 MW); LACTOCOCCUS LACTIS; LARICIFOMES OFFICINALIS FRUITING BODY; SODIUM METABISULFITE; PENTYLENE GLYCOL; SODIUM CHLORIDE; NIACINAMIDE

Tula Skincare Clear It Up Acne Clearing and Tone Correcting Gel

Drug Facts

Active ingredients

Salicylic Acid 2%

Purpose

Acne Treatment

Uses

- For treatment of acne

WARNINGS

For external use only.

When using this product

• skin irritation and dryness is more likely to occur if you use another topical acne medication at the same time. If irritation occurs, only use one topical acne medication at a time.

Keep out of reach of children.

If swallowed, get medical help or contact a Poison Control Center right away.

Stop use and ask a doctor if skin irritation occurs/gets worse.

Directions

- Clean the skin thoroughly before applying this product
- Cover the entire affected area with a thin layer one to three times daily
- Because excessive drying of the skin may occur, start with one application daily, then gradually increase to two or three uses daily if needed or as directed by a doctor
- If bothersome dryness or peeling occurs, reduce application to once a day or every other day.

INACTIVE INGREDIENT

WATER, SODIUM PCA, GLYCERIN, SODIUM POLYACRYLATE, POLYACRYLATE CROSSPOLYMER-6, NIACINAMIDE, LACTOCOCCUS FERMENT LYSATE, AZELAIC ACID, INULIN, FOMES OFFICINALIS (MUSHROOM) EXTRACT, BUTYLENE GLYCOL, SODIUM HYALURONATE, ALLANTOIN, LACTIC ACID, PEUMUS BOLDUS LEAF EXTRACT, EPILOBIUM ANGUSTIFOLIUM FLOWER/LEAF/STEM EXTRACT, ZINC PCA, BISABOLOL, FRUCTOSE, SODIUM METABISULFITE, PEG-40 HYDROGENATED CASTOR OIL, PENTYLENE GLYCOL, SODIUM CHLORIDE, SODIUM BENZOATE, XANTHAN GUM, ETHYLHEXYLGLYCERIN, PHENOXYETHANOL

Questions or Comments?:

1-844-545-1236

Made in the USA from local & globally sourced materials

DIST. BY: TULA LIFE, INC. NY, NY 10003

#1021E TULA.COM

PRINCIPAL DISPLAY PANEL - 30 mL carton

Tula Skincare

clear it up

acne clearing &

tone correction gel

salicylic acid

acne treatment

30 mL (1 FL OZ)